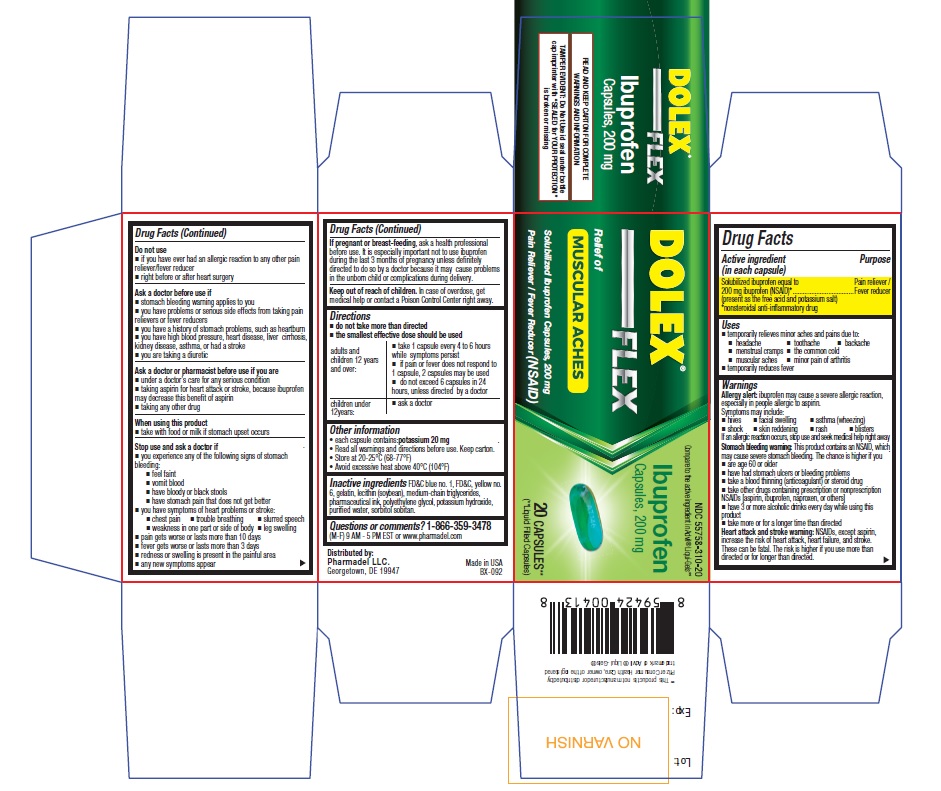 DRUG LABEL: Dolex Flex
NDC: 55758-310 | Form: CAPSULE, LIQUID FILLED
Manufacturer: Pharmadel LLC
Category: otc | Type: HUMAN OTC DRUG LABEL
Date: 20230913

ACTIVE INGREDIENTS: IBUPROFEN 200 mg/1 1
INACTIVE INGREDIENTS: SORBITAN; FD&C BLUE NO. 1; WATER; FD&C YELLOW NO. 6; SORBITOL; MEDIUM-CHAIN TRIGLYCERIDES; POTASSIUM HYDROXIDE; POLYETHYLENE GLYCOL, UNSPECIFIED; LECITHIN, SOYBEAN; GELATIN

DOLEX FLEX (Deactivated)

Active Ingredient

Active ingredient (in each capsule) | Purpose
Solubilized ibuprofen equal to 200 mg ibuprofen (NSAID)*............... | Pain reliever/fever reducer

* nonsteroidal anti-inflammatory drug

Uses

Temporarily relieves minor aches and pains due to:

- headache
- muscular aches
- minor pain of arthritis
- toothache
- backache
- the common cold
- menstrual cramps
- temporarily reduces fever

Warnings

Allergy alert:

Ibuprofen may cause a severeallergic reaction, especially in people allergic to aspirin. Symptoms may include:

- hives
- facial swelling
- asthma (wheezing)
- shock
- skin reddening
- rash
- blisters

If an allergic reaction occurs, stop use and seek
medical help right away.

Stomach bleeding warning:

This product contains an NSAID, which may cause severe stomach bleeding. The chance is higher if you:

- are age 60 or older
- have had stomach ulcers or bleeding problems
- take a blood thinning (anticoagulant) or steroid drug
- take other drugs containing prescription or nonprescription NSAIDs (aspirin, ibuprofen, naproxen, or others)
- have 3 or more alcoholic drinks every day while using this product
- take more or for a longer time than directed

Heart attack and stroke warning:

NSAIDs, except aspirin, increase the risk of heart attack, heart failure, and stroke. These can be fatal. The risk is higher if
you use more than directed or for longer than directed.

Do not use

- if you have ever had an allergic reaction to any other pain reliever/fever reducer
- right before or after heart surgery

Ask a doctor before use if

- stomach bleeding warning applies to you
- you have problems or serious side effects from taking pain relievers or fever reducers
- you have a history of stomach problems, such as heartburn
- you have high blood pressure, heart disease, liver cirrhosis, kidney disease, asthma, or had a stroke
- you are taking a diuretic

Ask a doctor or pharmacist before use if you are

- under a doctor’s care for any serious condition
- taking aspirin for heart attack or stroke, because ibuprofen may decrease this benefit of aspirin
- taking any other drug

When using this product

- take with food or milk if stomach upset occurs

If pregnant or breast-feeding,

ask a health
professional before use. It is especially important
not to use ibuprofen during the last 3 months of
pregnancy unless definitely directed to do so by
a doctor because it may cause problems in the
unborn child or complications during delivery.
Keep out of reach of children. In case of
overdose, get medical help or contact a Poison
Control Center right away (1-800-222-1222).

Keep out of reach of children.

In case of overdose, get medical help or contact a Poison Control Center right away.

Directions

- do not take more than directed
- the smallest effective dose should be used
- adults and children 12 years and over:
- take 1 capsule every 4 to 6 hours while symptoms persist
- if pain or fever does not respond to 1 capsule, 2 capsules may be used
- do not exceed 6 capsules in 24 hours, unless directed by a doctor
- children under 12 years: ask a doctor

Other information

- each capsule contains: potassium 20 mg
- store at 20-25°C (68-77°F)
- avoid excessive heat above 40°C (104°F)
- read all warnings and directions before use
- retain carton for complete product information and warnings

Inactive ingredients

FD&C blue no. 1, FD&C, yellow no.6, gelatin, lecithin (soybean), medium-chain triglycerides, pharmaceutical ink, polyethylene glycol, potassium hydroxide, purified water, sorbitol sobitan.

Questions or comments?

1-866-359-3478
(M-F) 9 AM - 5 PM EST or www.pharmadel.com

Package Principal Display Panel

DOLEX® FLEX

Relief of

MUSCULAR ACHES

Solubilized Ibuprofen Capsules, 200 mg
Pain Reliever / Fever Reducer (NSAID)

20 SOFTGELS**
(**Liquid Filled Capsules)